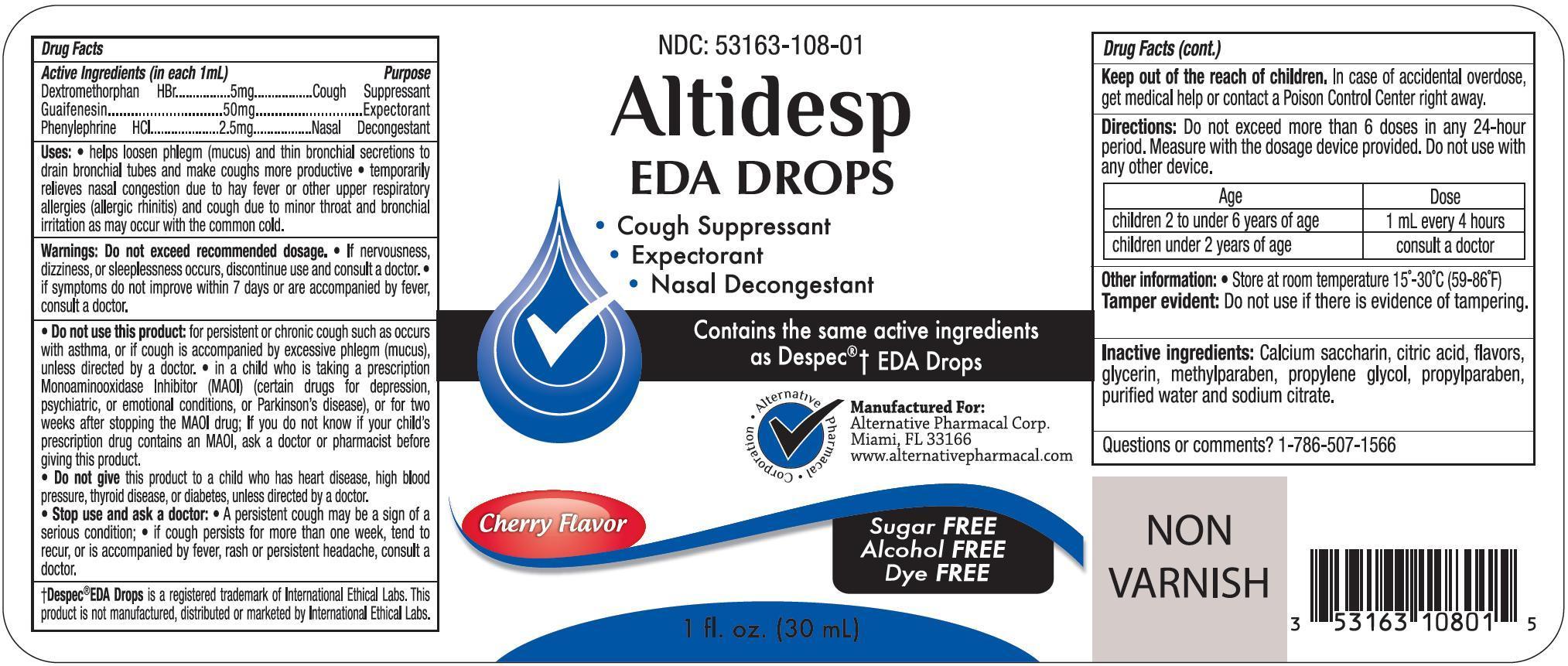 DRUG LABEL: Altidesp
NDC: 53163-108 | Form: SOLUTION/ DROPS
Manufacturer: Alternative Pharmacal Corporation
Category: otc | Type: HUMAN OTC DRUG LABEL
Date: 20241223

ACTIVE INGREDIENTS: DEXTROMETHORPHAN HYDROBROMIDE 5 mg/1 mL; GUAIFENESIN 50 mg/1 mL; PHENYLEPHRINE HYDROCHLORIDE 2.5 mg/1 mL
INACTIVE INGREDIENTS: SACCHARIN CALCIUM; ANHYDROUS CITRIC ACID; GLYCERIN; METHYLPARABEN; POLYETHYLENE GLYCOL, UNSPECIFIED; PROPYLPARABEN; WATER; SODIUM CITRATE

Alt- AltidespEDADr 108

Active Ingredients (in each 1 mL) Purpose

Dextromethorphan HBr............ 5 mg............. Cough Suppressant

Guaifenesin.......................... 50 mg............. Expectorant

Phenylephrine HCl................ 2.5 mg.............. Nasal Decongestant

PURPOSE

Cough Suppressant

Expectorant

Nasal Decongestant

Uses

- helps loosen phlegm (mucus) and thin bronchial secretions to drain bronchial tubes and make coughs more productive
- temporarily relieves nasal congestion due to hay fever or other upper respiratory allergies (allergic rhinitis) and cough due to minor throat and bronchial irritation as may occur with the common cold.

Warnings

Do not exceed recommended dosage

If nervousness, dizziness, or sleeplessness occurs, discontinue use and consult a doctor. If symptoms do not improve within 7 days or are accompanied by fever, consult a doctor.

Do not use this product: for persistent or chrnoic cough such as occurs with asthma, or if cough is accompanied by excessive phlegm (mucus), unless directed by a doctor.

In a chlid who is taking a prescription Monoaminooxidase Inhibito (MAOI) (certain drugs for depression, psychiatric, or emotional conditions, or Parkinson's disease), or for two weeks after stopping the MAOI drug; If you do not know if your child's prescription drug contains an MAOI, ask a doctor or phamacist before giving this product.

Do not give this product to a child who has heart disease, high blood pressure, thyroid disease, or diabetes, unless directed by a doctor.

Stop use and ask a doctor before use if:

- A persistent cough may be a sign of a serious condition
- If cough persists for more than one week, tend to recur, or is accompanied by fever, rash or persistent heachache, consult a doctor.

PREGNANCY OR BREAST FEEDING

If pregnant or breast-feeding, ask a health profession before use.

Keep out of reach of children. In case of overdose, get medical help or contact a Poison Control Center right away.

Directions

- Do not use more than 6 doses in any 24 hour period
- Measure with dosage device provided. Do not use with any other device

Age | Dose
Children 2 years to under 6 years of age | 1 mL every 4 hours
Children under 2 years of age | consult a doctor

Other Information

Store at room temperature 15^0 - 30^0C (59^0-86^0F)

Tamper Evident Feature: Do not use if seal is torn, broken or missing.

INACTIVE INGREDIENT

Inactiveingredients

calcium saccharin, citric acid, flavors, glycerin, methylparaben, propylene glycol, propylparaben, purified water and sodium citrate

Questions or comments? 1-786-507-1566